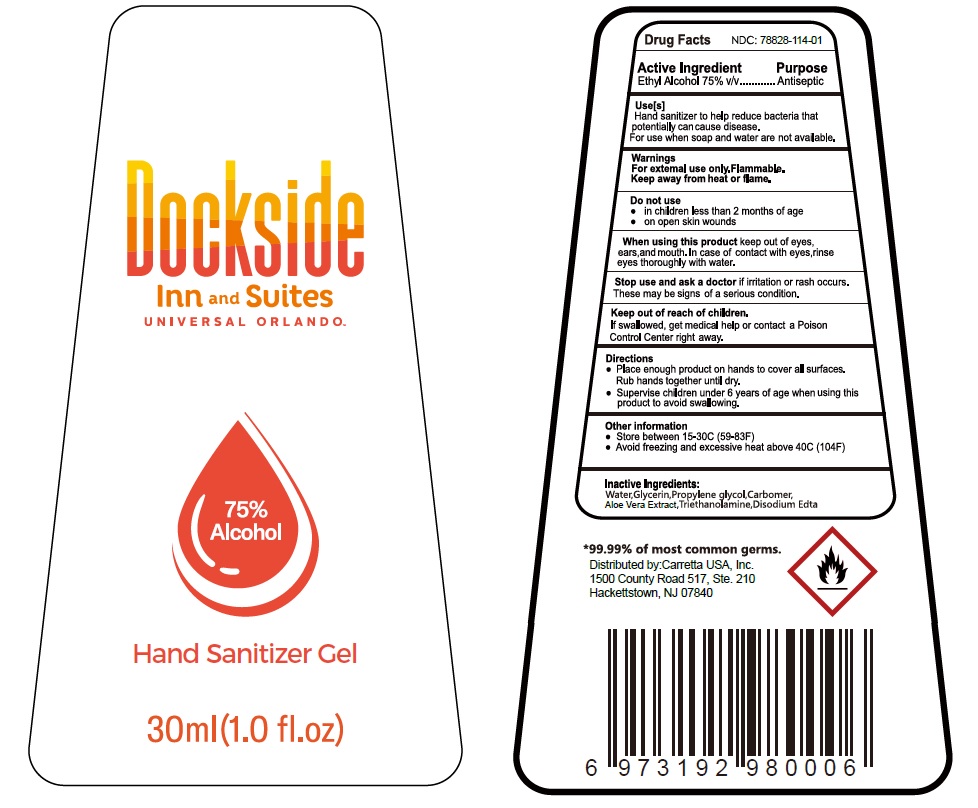 DRUG LABEL: Dockside Inn and Suites Universal Orlando Hand Sanitizer Gel
NDC: 78828-114 | Form: GEL
Manufacturer: Carretta USA, Inc
Category: otc | Type: HUMAN OTC DRUG LABEL
Date: 20200613

ACTIVE INGREDIENTS: ALCOHOL 0.75 mL/1 mL
INACTIVE INGREDIENTS: WATER; GLYCERIN; PROPYLENE GLYCOL; CARBOMER HOMOPOLYMER, UNSPECIFIED TYPE; ALOE VERA LEAF; TROLAMINE; EDETATE DISODIUM ANHYDROUS

Dockside Inn & Suites Universal Orlando Hand Sanitizer Gel

Active Ingredient

Ethyl Alcohol 75% v/v

Purpose

Antiseptic

Uses[s]

Hand sanitizer to help reduce bacteria that potentially can cause disease.

For use when soap and water are not available.

Warnings

For external use only.Flammable.

Keep away from heat or flame.

Do not use

- in children less than 2 months of age
- on open skin wounds

When using this product keep out of eyes, ears,and mouth. In case of contact with eyes,rinse eyes thoroughly with water.

Stop use and ask a doctor if irritation or rash occurs. These may be signs of a serious condition.

Keep out of reach of children.

If swallowed, get medical help or contact a Poison Control right away.

Directions

- Place enough product on hands to cover all surfaces. Rub hands together until dry.
- Supervise children under 6 years of age when using this product to avoid swallowing.

Other information

- Store between 15-30C (59-83F)
- Avoid freezing and excessive heat above 40C (104F)

Inactive Ingredients:

Water,Glycerin,Propylene glycol,Carbomer,Aloe Vera Extract,Triethanolamine,Disodium Edta

*99.99% of most common germs.

Distributed by:Carretta USA, Inc.

1500 County Road 517, Ste. 210

Hackettstown, NJ 07840